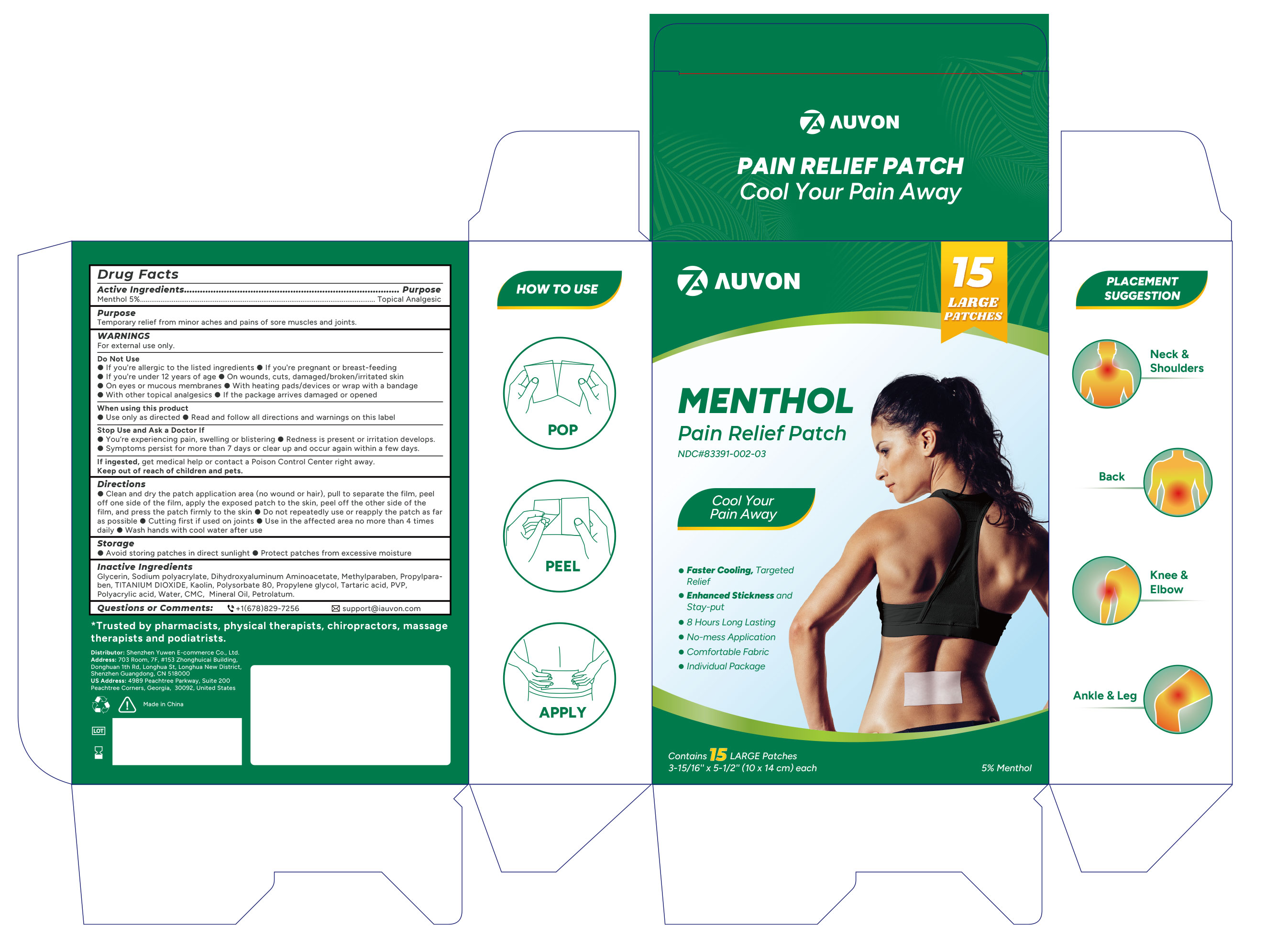 DRUG LABEL: AUVON Pain Relief
NDC: 83391-002 | Form: PATCH
Manufacturer: SHENZHEN YUWEN E-COMMERCE CO., LTD.
Category: otc | Type: HUMAN OTC DRUG LABEL
Date: 20241208

ACTIVE INGREDIENTS: MENTHOL 470 mg/1 1
INACTIVE INGREDIENTS: DIHYDROXYALUMINUM AMINOACETATE ANHYDROUS; CARBOXYMETHYLCELLULOSE; GLYCERIN; METHYLPARABEN; SODIUM POLYACRYLATE (2500000 MW); POLYSORBATE 80; PROPYLENE GLYCOL; TARTARIC ACID; TITANIUM DIOXIDE; WATER; PROPYLPARABEN; KAOLIN; POLYACRYLIC ACID (250000 MW); PETROLATUM; MINERAL OIL

83391-002

MENTHOL AUVON Pain Relief Patch

Drug Facts

Active ingredients

Menthol 5%

Purposes

Topical Analgestic

Use

Temporary relief from minor aches and paons of sore muscles and joints

Warnings

For external use only

Do not use

- If you are allergic to the listed ingredients
- If you are pregnent or breast feeding
- If you are under 12 years of age
- On wounds, cuts, damaged/broken/irritated skin
- On eyes or mucous membranes
- With heating pads/devices or wrap with a bandage
- With other topical analgesics
- If the package arrives damaged or opened.

When using this product

■ Use only as directed

■ Read and follow all directions and warnings on this label

Stop use and ask a doctor if

You are experiencing pain, swelling or blistering

Redness is persent or irritation develops

Symptoms persist for more than 7 days or clear up and occur again within a few days

Keep outof reach of children and pets.

If ingested, get medical help or contact a Poison Control Center

right away.

Directions

■ Clean and dry the patch application area (no wound or hair), pull to separate the film, peel off one side of the film, apply the exposed patch to the skin, peel off the other side of the film, and press the patch firmly to the skin.

■ Do not repeatedly use or repeatedly reapply the patch as far as possible

■ Cut first if if used on joints

■ Use in te affected area no more than 4 times daily

■ Wash hands with cool water after use

Storage

- Avoid storing patches in direct sunlight
- Protect patches from excessive moisture

Inactive ingredients

Glycerin, sodium polyacrylate, dihydroxyaluminum aminoacetate, methylparaben, propylparaben, polyacrylic acid, Kaolin, polysorbate 80, propylene glycol, tartaric acid, PVP, titanium dioxide, water, CMC, mineral oil, petrolatum,